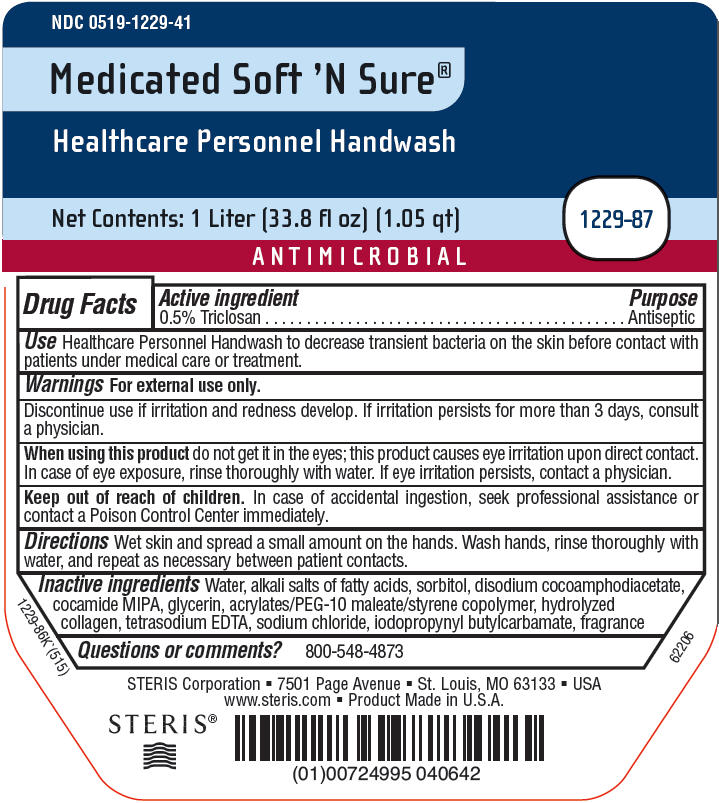 DRUG LABEL: Medicated Soft N Sure 
NDC: 0519-1229 | Form: LIQUID
Manufacturer: STERIS Corporation
Category: otc | Type: HUMAN OTC DRUG LABEL
Date: 20150601

ACTIVE INGREDIENTS: Triclosan 0.5 g/1000 mL
INACTIVE INGREDIENTS: WATER; SORBITOL; DISODIUM COCOAMPHODIACETATE; COCO MONOISOPROPANOLAMIDE; GLYCERIN; EDETATE SODIUM; METHACRYLATE/METHOXY PEG-10 MALEATE/STYRENE COPOLYMER; GELATIN HYDROLYSATE (PORCINE SKIN, MW 3000); SODIUM CHLORIDE; IODOPROPYNYL BUTYLCARBAMATE

Medicated Soft 'N Sure®
Healthcare Personnel Handwash

Drug Facts

Active ingredient

0.5% Triclosan

Purpose

Antiseptic

Use

Healthcare Personnel Handwash to decrease transient bacteria on the skin before contact with patients under medical care or treatment.

Warnings

For external use only.

DO NOT USE

Discontinue use if irritation and redness develop. If irritation persists for more than 3 days, consult a physician.

When using this product do not get it in the eyes; this product causes eye irritation upon direct contact. In case of eye exposure, rinse thoroughly with water. If eye irritation persists, contact a physician.

Keep out of reach of children. In case of accidental ingestion, seek professional assistance or contact a Poison Control Center immediately.

Directions

Wet skin and spread a small amount on the hands. Wash hands, rinse thoroughly with water, and repeat as necessary between patient contacts.

Inactive ingredients

Water, alkali salts of fatty acids, sorbitol, disodium cocoamphodiacetate, cocamide MIPA, glycerin, acrylates/PEG-10 maleate/styrene copolymer, hydrolyzed collagen, tetrasodium EDTA, sodium chloride, iodopropynyl butylcarbamate, fragrance

Questions or comments?

800-548-4873

PRINCIPAL DISPLAY PANEL - 1 Liter Bottle Label

NDC 0519-1229-41

Medicated Soft 'N Sure®

Healthcare Personnel Handwash

Net Contents: 1 Liter (33.8 fl oz) (1.05 qt)

1229-87

ANTIMICROBIAL